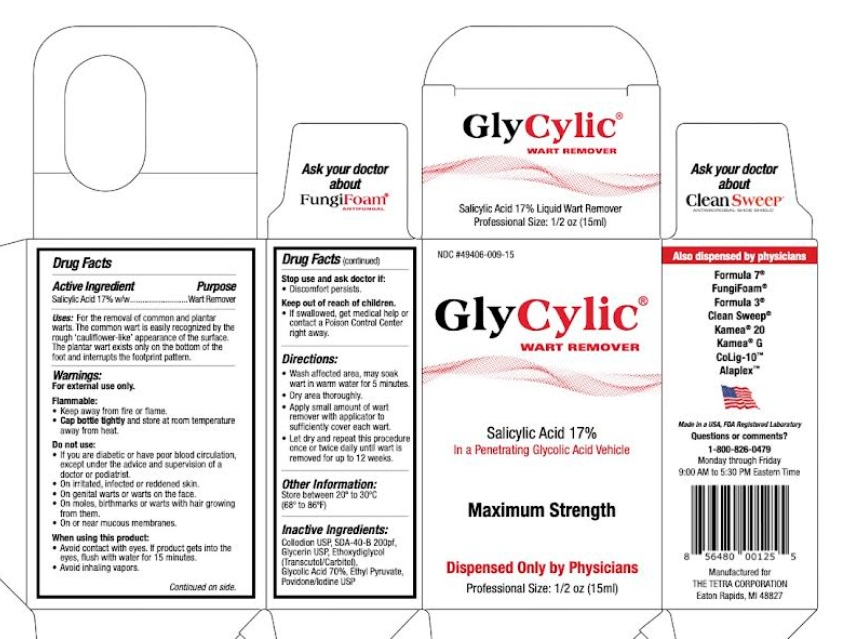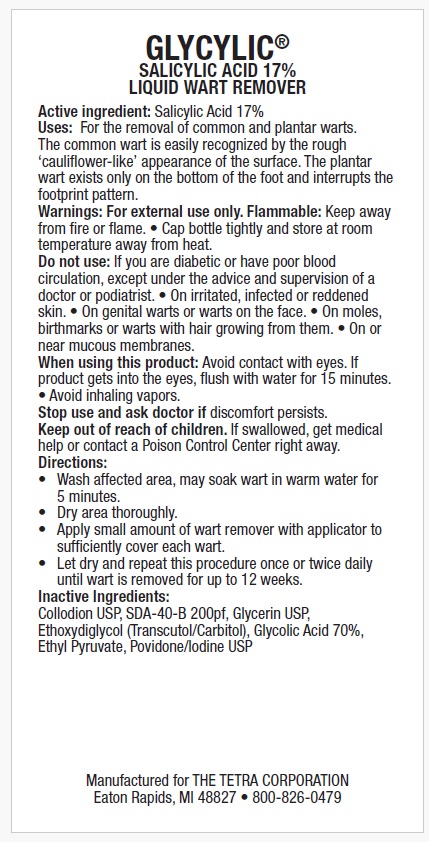 DRUG LABEL: GlyCylic
NDC: 49406-009 | Form: LIQUID
Manufacturer: The Tetra Corporation
Category: otc | Type: HUMAN OTC DRUG LABEL
Date: 20250818

ACTIVE INGREDIENTS: SALICYLIC ACID 17 g/100 mL
INACTIVE INGREDIENTS: GLYCERIN; DIETHYLENE GLYCOL MONOETHYL ETHER; IODINE; GLYCOLIC ACID; ETHYL PYRUVATE; ALCOHOL; PYROXYLIN

Active Ingredient

Salicylic Acid 17%

Purpose

Wart Remover

Uses

for the removal of common and plantar warts. The common wart is easily recognized by the rough 'cauliflower-like' appearance of the surface. The plantar wart exists only on the bottom of the foot and interrupts footprint pattern.

Warnings

FOR EXTERNAL USE ONLY.

Flammable
• keep away from fire or flame.
• cap bottle tightlyand store at room temperature away from heat.

Do not use
• if you are a diabetic or have poor blood circulation, except under the advice and supervision of a doctor or podiatrist.
• irritated, infected or reddened skin.
• genital warts and warts on the face.
• moles, birthmarks and warts with hair growing from them.
• mucous membranes.

When using this product
• avoid contact with eyes. If product gets into the eyes, flush with water for 15 minutes.
• avoid inhaling vapors.

Stop use and ask doctor if
• discomfort persists.

Keep out of reach of children

If swallowed, get medical help or contact a Poison Control Center right away.

Directions

• wash affected area, may soak wart in warm water for 5 minutes

• dry area thoroughly

• apply small amount of wart remover with applicator to sufficiently cover each wart

• let dry and repeat this procedure once or twice daily until wart is removed for up to 12 weeks

Inactive ingredients

Collodion USP, SDA-40-B 200pf, Glycerin USP, Ethoxydiglycol (Transcutol/Carbitol), Glycolic Acid 70%, Ethyl Pyruvate, Povidone/Iodine USP